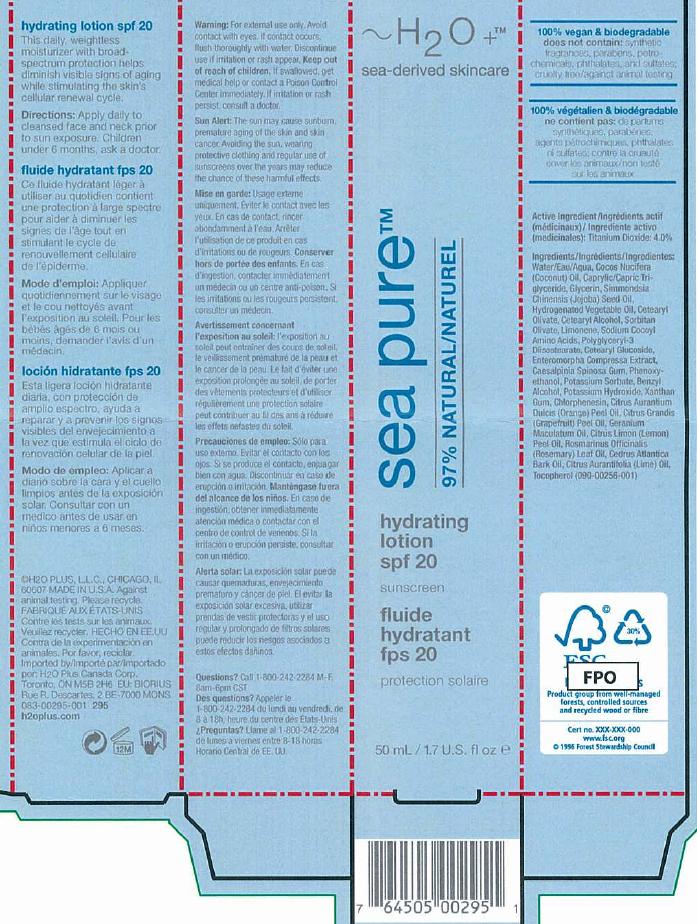 DRUG LABEL: Sea Pure Hydrating
NDC: 65903-295 | Form: LOTION
Manufacturer: H2O PLUS
Category: otc | Type: HUMAN OTC DRUG LABEL
Date: 20110929

ACTIVE INGREDIENTS: Titanium Dioxide 40 uL/1 mL
INACTIVE INGREDIENTS: water; COCONUT OIL; GLYCERIN; MEDIUM-CHAIN TRIGLYCERIDES; CORN OIL; JOJOBA OIL; CETEARYL OLIVATE; CETOSTEARYL ALCOHOL; LIMONENE, (-)-; SORBITAN OLIVATE; BENZYL ALCOHOL; PHENOXYETHANOL; POLYGLYCERYL-4 ISOSTEARATE; CETEARYL GLUCOSIDE; XANTHAN GUM; ULVA COMPRESSA; POTASSIUM HYDROXIDE; CITRUS SINENSIS FLOWER OIL; TOCOPHEROL; CAESALPINIA SPINOSA RESIN; CITRUS MAXIMA FRUIT RIND OIL; PELARGONIUM GRAVEOLENS FLOWER OIL; LEMON OIL; ROSEMARY OIL; JUNIPERUS DEPPEANA WOOD OIL; LIME OIL

Drug Facts

ACTIVE INGREDIENT

Titanium Dioxide4.0%

WHEN USING

Helps prevent sunburns
If used as directed with other sun protection measure (see directions)decreases the risk of skin
cancers/ and early skin aging

WARNINGS

For external use only
Do not use on damaged or broken skin
Stop use and ask a doctor is a rash occurs
When using this product* keep out of eyes, Rinse with water to remove.
Keep out of reach of children. If swallowed, get medical help or contact a Poison control center right
away

DOSAGE AND ADMINISTRATION

For Sunscreen Use
Apply Liberally
Children under six months of age: Ask a doctor

STORAGE AND HANDLING

Protect this product in this container from excessive heat and direct sunlight

INACTIVE INGREDIENT

Enter section text here

Image of carton label sphl295.jpg